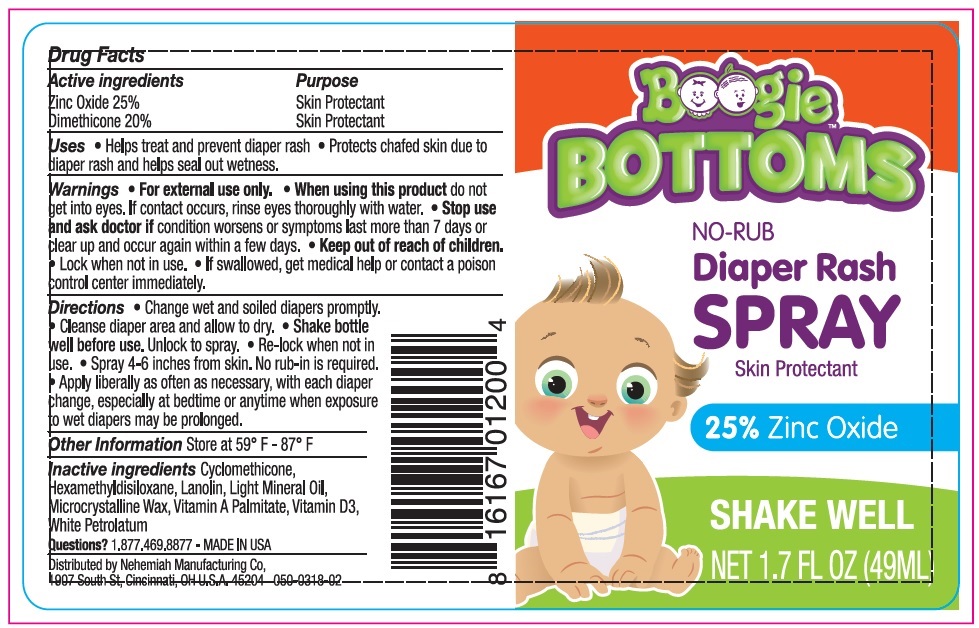 DRUG LABEL: Boogie Bottoms
NDC: 79747-003 | Form: SPRAY
Manufacturer: ELEEO BRANDS LLC		
Category: otc | Type: HUMAN OTC DRUG LABEL
Date: 20240302

ACTIVE INGREDIENTS: DIMETHICONE 200 mg/1 mL; ZINC OXIDE 250 mg/1 mL
INACTIVE INGREDIENTS: CYCLOMETHICONE; HEXAMETHYLDISILOXANE; LANOLIN; MINERAL OIL; MICROCRYSTALLINE WAX; PETROLATUM; VITAMIN A PALMITATE; CHOLECALCIFEROL; .ALPHA.-TOCOPHEROL, DL-; CORN OIL

Boogie Bottoms™

Drug Facts

ACTIVE INGREDIENT

Active ingredients | Purpose
Zinc Oxide 25% | Skin Protectant
Dimethicone 20% | Skin Protectant

Uses

- Helps treat and prevent diaper rash
- Protects chafed skin due to diaper rash and helps seal out wetness.

Warnings

- For external use only.

- When using this product do not get into eyes. If contact occurs, rinse eyes thoroughly with water.

- Stop use and ask doctor if condition worsens or symptoms last more than 7 days or clear up and occur again within a few days.

- Keep out of reach of children.
- Lock when not in use.
- If swallowed, get medical help or contact a poison control center immediately.

Directions

- Change wet and soiled diapers promptly.
- Cleanse diaper area and allow to dry.
- Shake bottle well before use. Unlock to spray.
- Re-lock when not in use.
- Spray 4-6 inches from skin. No rub-in is required.
- Apply liberally as often as necessary, with each diaper change, especially at bedtime or anytime when exposure to wet diapers may be prolonged.

Other Information

Store at 59° F - 87° F

Inactive ingredients

Cyclomethicone, Hexamethyldisiloxane, Lanolin, Light Mineral Oil, Microcrystalline Wax, Vitamin A Palmitate, Vitamin D3, White Petrolatum

Questions?

1.877.469.8877 - MADE IN USA

Distributed by Nehemiah Manufacturing Co,
1907 South St, Cincinnati, OH U.S.A. 45204

PRINCIPAL DISPLAY PANEL - 49 ML Bottle Label

NEW!
NDC 79747-003-01

Boogie
BOTTOMS™

No-Rub
Diaper Rash Spray
Skin Protectant

SHAKE
WELL

Treats & Prevents diaper rash

Spray-on application

Fast & Easy to use

25% Zinc Oxide

Free from:
fragrances • dyes • parabens

NET 1.7 FL OZ (49ML)